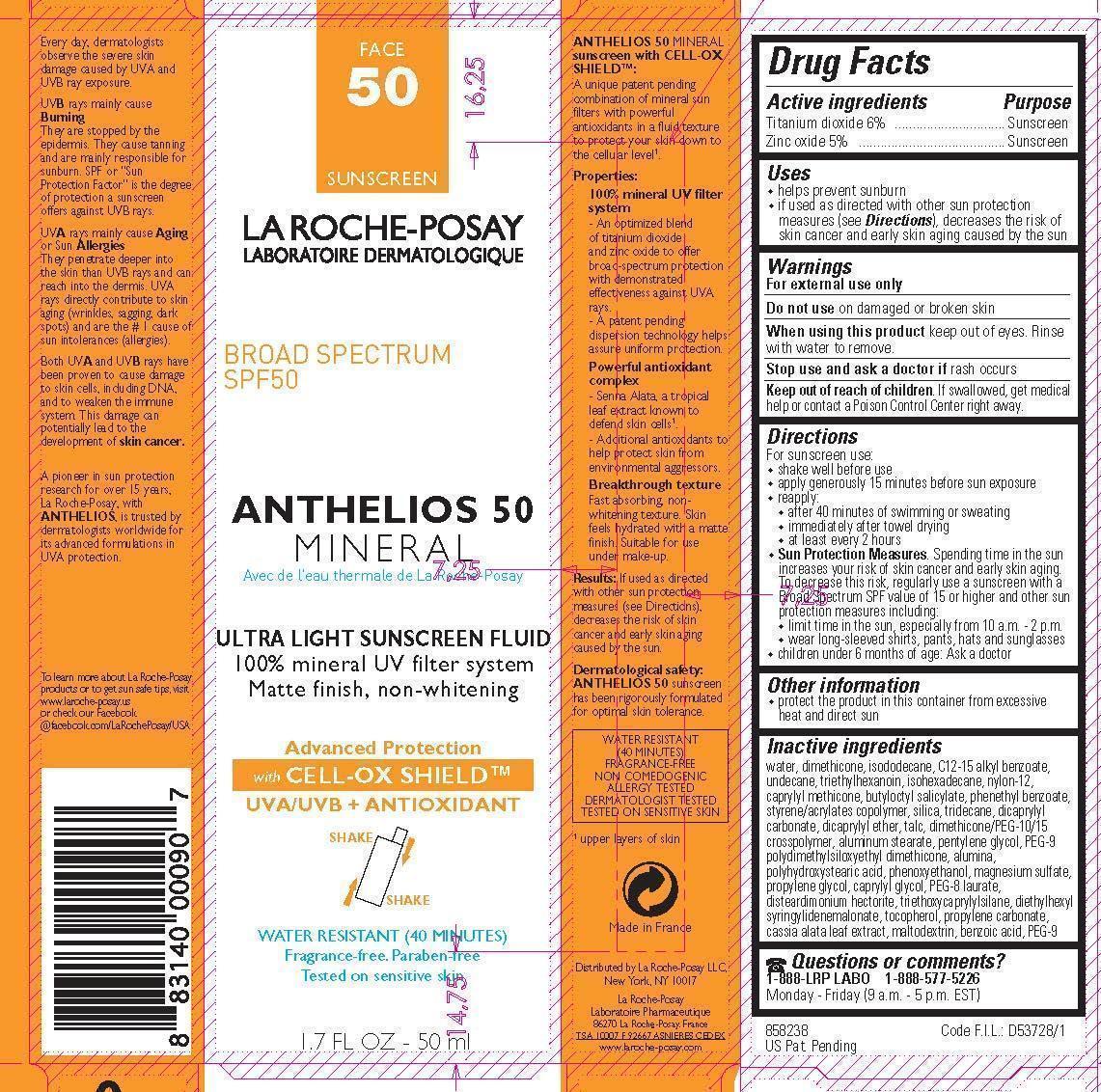 DRUG LABEL: La Roche Posay Laboratoire Dermatologique Anthelios 50 Mineral Ultra Light Broad Spectrum SPF 50 Sunscreen
NDC: 69625-908 | Form: LOTION
Manufacturer: Cosmetique Active Production
Category: otc | Type: HUMAN OTC DRUG LABEL
Date: 20231213

ACTIVE INGREDIENTS: Titanium dioxide 60 mg/1 mL; Zinc oxide 50 mg/1 mL
INACTIVE INGREDIENTS: WATER; DIMETHICONE; ISODODECANE; ALKYL (C12-15) BENZOATE; UNDECANE; TRIETHYLHEXANOIN; ISOHEXADECANE; NYLON-12; CAPRYLYL TRISILOXANE; BUTYLOCTYL SALICYLATE; PHENETHYL BENZOATE; STYRENE/ACRYLAMIDE COPOLYMER (MW 500000); SILICON DIOXIDE; TRIDECANE; DICAPRYLYL CARBONATE; DICAPRYLYL ETHER; TALC; ALUMINUM STEARATE; PENTYLENE GLYCOL; PEG-9 POLYDIMETHYLSILOXYETHYL DIMETHICONE; ALUMINUM OXIDE; POLYHYDROXYSTEARIC ACID (2300 MW); PHENOXYETHANOL; MAGNESIUM SULFATE, UNSPECIFIED FORM; PROPYLENE GLYCOL; CAPRYLYL GLYCOL; PEG-8 LAURATE; DISTEARDIMONIUM HECTORITE; TOCOPHEROL; PROPYLENE CARBONATE; MALTODEXTRIN; BENZOIC ACID; POLYETHYLENE GLYCOL 450

Drug Facts

Active ingredients

Titanium Dioxide 6%

Zinc Oxide 5%

Purpose

Sunscreen

Uses

- helps prevent sunburn
- if used as directed with other sun protection measures (see Directions), decreases the risk of skin cancer and early skin aging caused by the sun

Warnings

For external use only

Do not use

on damaged or broken skin

When using this product

keep out of eyes. Rinse with water to remove.

Stop use and ask a doctor if

rash occurs

Keep out of reach of children.

If swallowed, get medical help or contact a Poison Control Center right away.

Directions

- shake well before use

- apply generously 15 minutes before sun exposure

- reapply:

- after 40 minutes of swimming or sweating

- immediately after towel drying

- at least every 2 hours

- Sun Protection Measures. Spending time in the sun increases your risk of skin cancer and early skin aging. To decrease this risk, regularly use a sunscreen with a Broad Spectrum SPF value of 15 or higher and other sun protection measures including:

- limit time in the sun, especially from 10 a.m. - 2 p.m.

- wear long-sleeved shirts, pants, hats and sunglasses

- children under 6 months of age: Ask a doctor

Other information

protect the product in this container from excessive heat and direct sun

Inactive ingredients

water, dimethicone, isododecane, C12-15 alkyl benzoate, undecane, triethylhexanoin, isohexadecane, nylon-12, caprylyl methicone, butyloctyl salicylate, phenethyl benzoate, styrene/acrylates copolymer, silica, tridecane, dicaprylyl carbonate, dicaprylyl ether, talc, dimethicone/PEG-10/15 crosspolymer, aluminum stearate, pentylene glycol, PEG-9 polydimethylsiloxyethyl dimethicone, alumina, polyhydroxystearic acid, phenoxyethanol, magnesium sulfate, propylene glycol, caprylyl glycol, PEG-8 laurate, disteardimonium hectorite, triethoxycaprylylsilane diethylhexyl syringylidenemalonate, tocopherol, propylene carbonate, cassia alata leaf extract, maltodextrin, benzoic acid, PEG-9

Questions or comments?

1-888-LRP LABO 1-888-577-5226

Monday - Friday (9 a.m. - 5 p.m. EST)